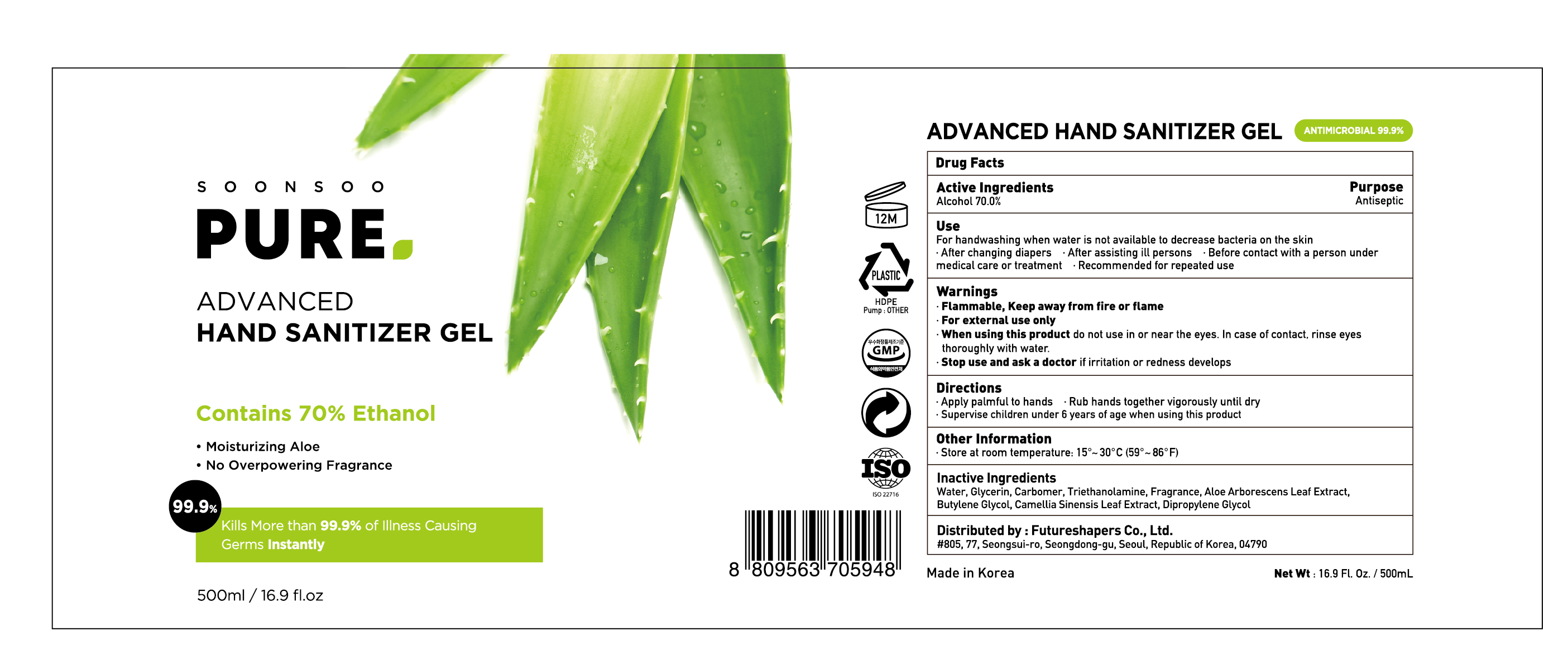 DRUG LABEL: Soonsoo Pure Advanced Hand Sanitizer Gel
NDC: 74004-910 | Form: GEL
Manufacturer: Ester Co., Ltd.
Category: otc | Type: HUMAN OTC DRUG LABEL
Date: 20200624

ACTIVE INGREDIENTS: ALCOHOL 350 mL/500 mL
INACTIVE INGREDIENTS: DIPROPYLENE GLYCOL; BUTYLENE GLYCOL; GREEN TEA LEAF; CARBOMER HOMOPOLYMER, UNSPECIFIED TYPE; WATER; TROLAMINE; GLYCERIN; ALOE VERA LEAF

[Ester Co., Ltd.-Soonsoo Pure Advanced Hand Sanitizer Gel] 500 ml in Bottle+Pump : 74004-910-01
Green